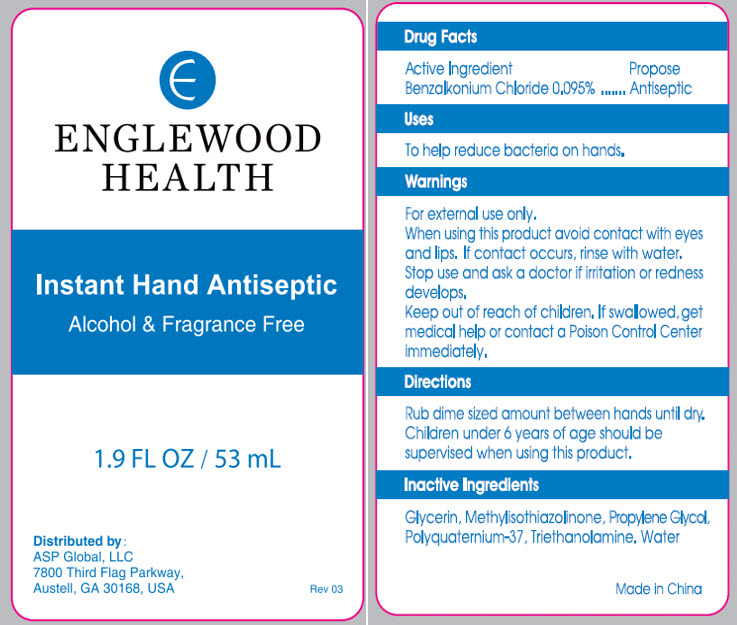 DRUG LABEL: Instant Hand Antiseptic
NDC: 59448-002 | Form: GEL
Manufacturer: ASP Global
Category: otc | Type: HUMAN OTC DRUG LABEL
Date: 20241205

ACTIVE INGREDIENTS: BENZALKONIUM CHLORIDE 0.095 mg/100 mL
INACTIVE INGREDIENTS: WATER; POLYQUATERNIUM-37 (25000 MPA.S); GLYCERIN; PROPYLENE GLYCOL; METHYLISOTHIAZOLINONE; TROLAMINE

Instant Hand Antiseptic

Drug Facts

Active Ingredient

Benzalkonium Chloride 0.095%

Purpose

Antiseptic

Uses

To help reduce bacteria on hands.

Warnings

For external use only.

When using this product avoid contact with eyes and lips. If contact occurs, rinse with water.

Stop use and ask a doctor if irritation or redness develops.

Keep out of reach of children.If swallowed, get medical help or contact a Poison Control Center immediately.

Directions

Rub dime sized amount between hands until dry.

Children under 6 years of age should be supervised when using this product.

Inactive Ingredients

Glycerin, Methylisothiazolinone, Propylene Glycol, Polyquaternium-37, Triethanolamine. Water

Distributed by :
ASP Global, LLC
7800 Third Flag Parkway,
Austell, GA 30168, USA

PRINCIPAL DISPLAY PANEL - 53 mL Bottle Label

ENGLEWOOD
HEALTH

Instant Hand Antiseptic

Alcohol & Fragrance Free

1.9 FL OZ / 53 mL

Distributed by :
ASP Global, LLC
7800 Third Flag Parkway,
Austell, GA 30168, USA

Rev 03